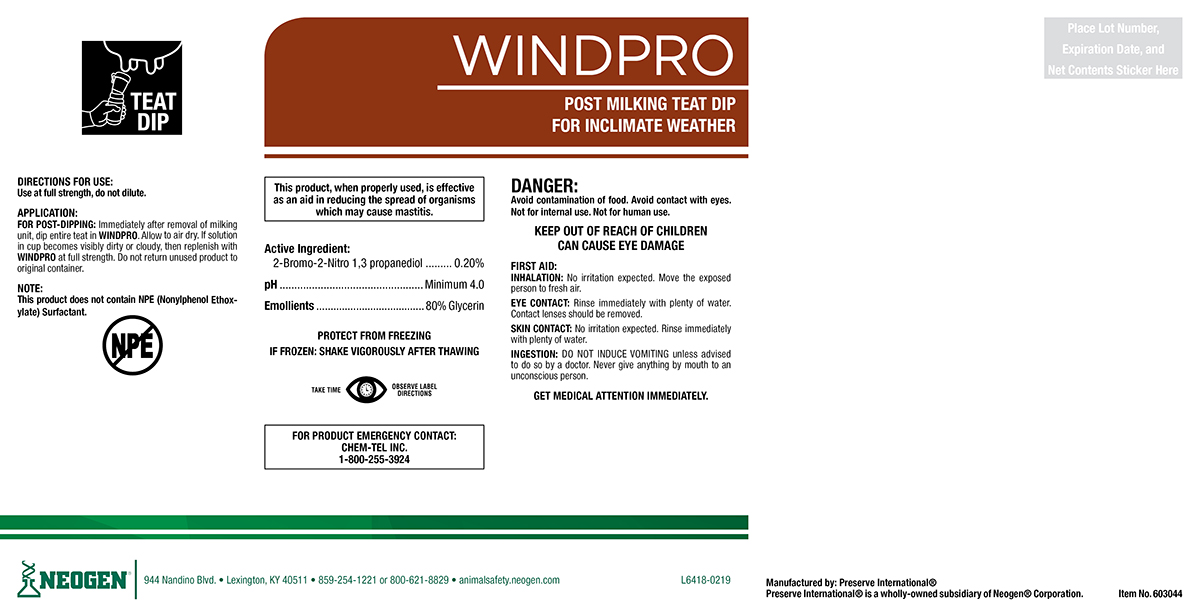 DRUG LABEL: Windpro
NDC: 60648-9016 | Form: SOLUTION
Manufacturer: Preserve International
Category: animal | Type: OTC ANIMAL DRUG LABEL
Date: 20190521

ACTIVE INGREDIENTS: BRONOPOL 2.16 g/1 L; GLYCERIN 432.38 g/1 L

WINDPRO

DIRECTIONS FOR USE:

Use at full strength, do not dilute.

APPLICATION:

FOR POST-DIPPING: Immediately after removal of milking unit, dip entire teat in WINDPRO. Allow to air dry. If solution in cup becomes visibly dirty or cloudy, then replenish with WINDPRO at full strength. Do not return unused product to original container.

NOTE:

This product does not contain NPE (Nonylphenol Ethoxylate) Surfactant.

WARNINGS AND PRECAUTIONS

PROTECT FROM FREEZING

IF FROZEN: SHAKE VIGOROUSLY AFTER THAWING

WARNINGS AND PRECAUTIONS

TAKE TIME OBSERVE LABEL DIRECTIONS

DANGER:

Avoid contamination of food. Avoid contact with eyes. Not for internal use. Not for human use.

KEEP OUT OF REACH OF CHILDREN

CAN CAUSE EYE DAMAGE

FIRST AID:

INHALATION: No irritation expected. Move the exposed person to fresh air.

EYE CONTACT: Rinse immediately with plenty of water. Contact lenses should be removed.

SKIN CONTACT: No irritation expected. Rinse immediately with plenty of water.

INGESTION: DO NOT INDUCE VOMITING unless advised to do so by a doctor. Never give anything by mouth to an unconscious person.
GET MEDICAL ATTENTION IMMEDIATELY.

FOR PRODUCT EMERGENCY CONTACT: Chem-Tel Inc. 1-800-255-3924

PACKAGE LABEL

WINDPRO

POST MILKING TEAT DIP FOR INCLIMATE WEATHER

This product, when properly used, is effective as an aid
in reducing the spread of organisms which may cause
mastitis.

Active Ingredien:

2-Bromo-2-Nitro 1,3 propanediol..........0.20%
pH.........................................................Minimum 4.0
Emollients.............................................80% Glycerin

Manufactured By: Preserve International®

Preserve International® is a wholly-owned subsidiary of Neogen® Corporation.

NEOGEN®

944 Nandino Blvd.

Lexington, KY 40511

859-254-1221 or 800-621-8829

animalsafety.neogen.com